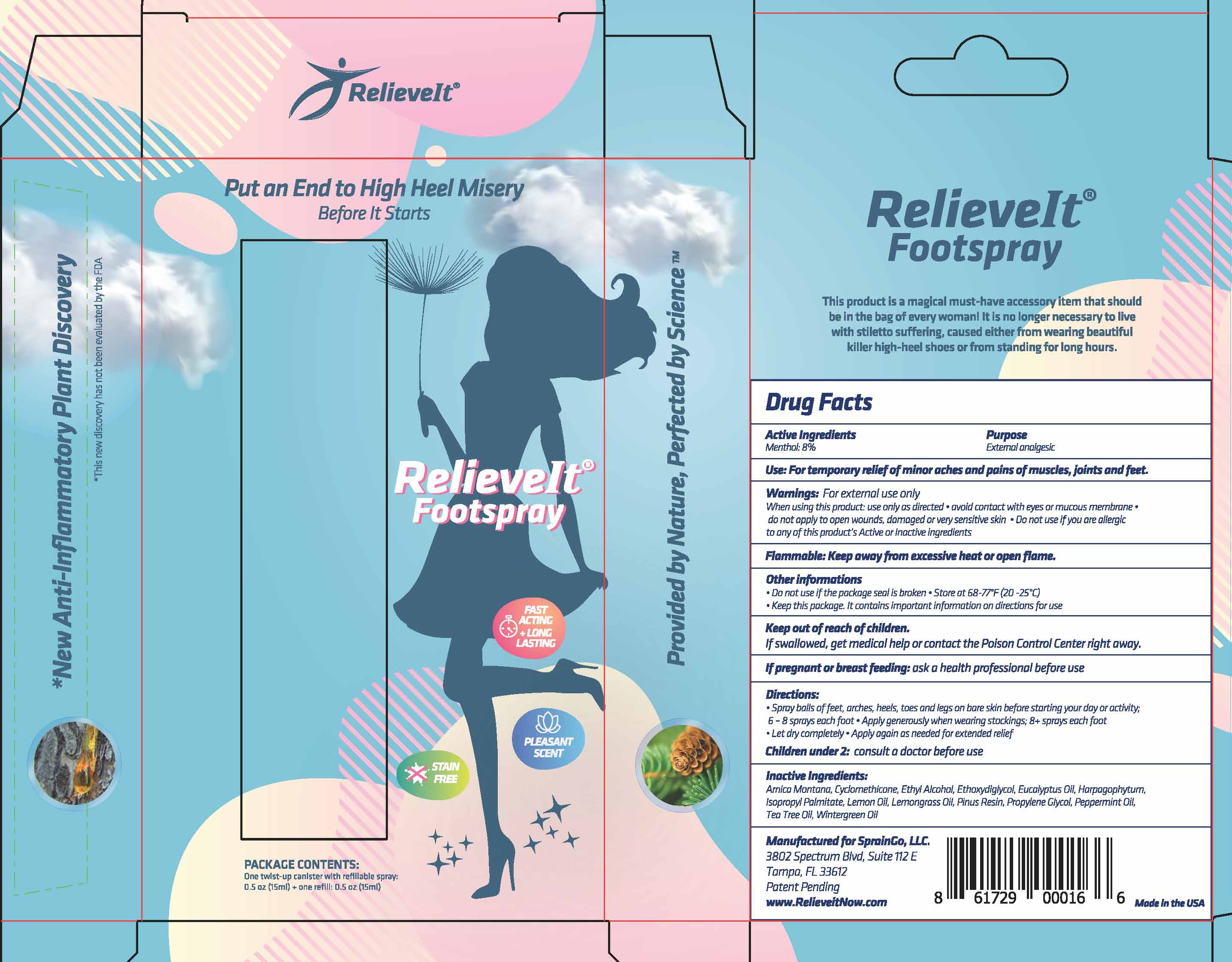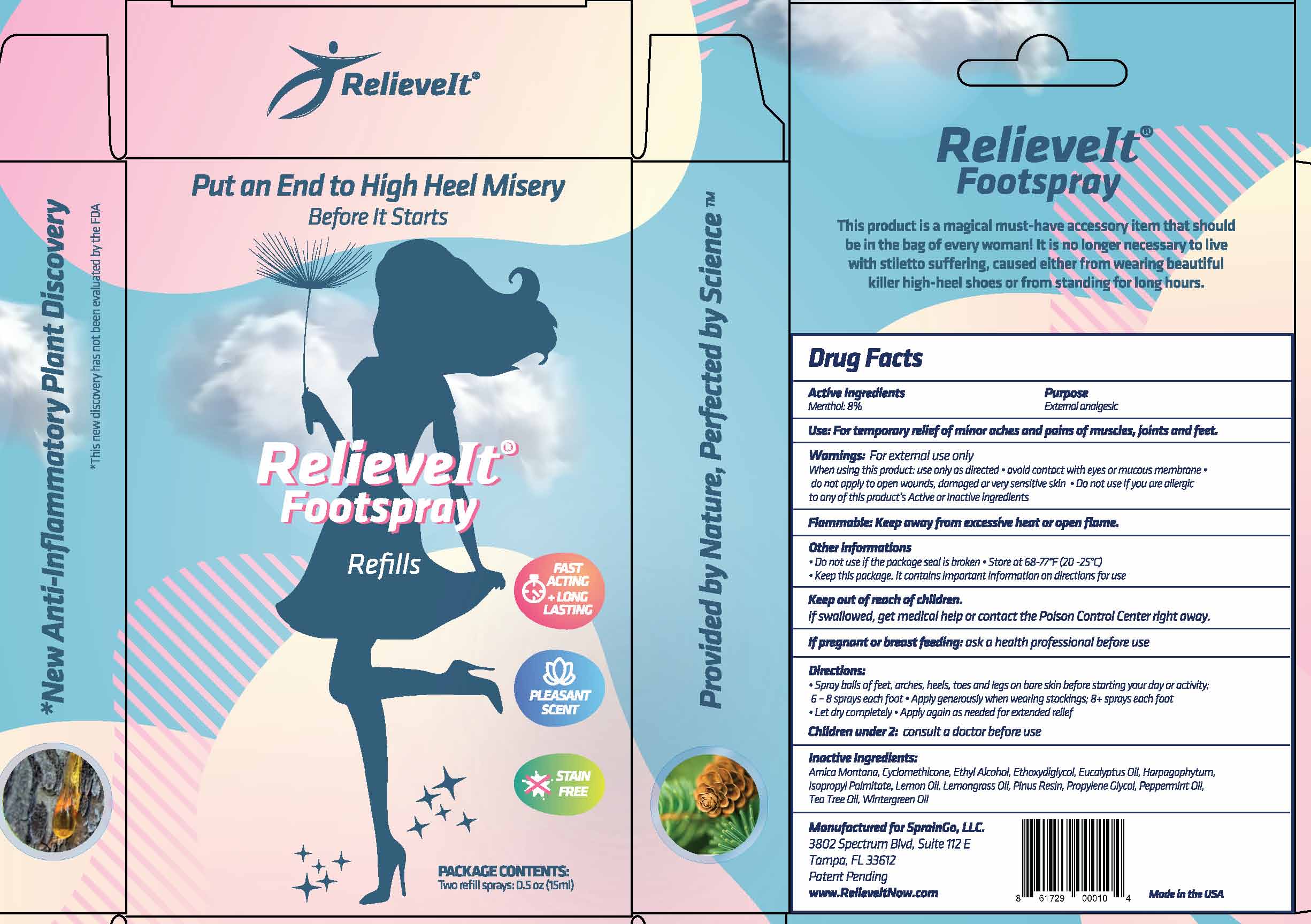 DRUG LABEL: RelieveIt Footspray
NDC: 58133-956 | Form: LIQUID
Manufacturer: Cosmetic Specialty labs, Inc.
Category: otc | Type: HUMAN OTC DRUG LABEL
Date: 20200313

ACTIVE INGREDIENTS: MENTHOL 1.2 mg/15 mL
INACTIVE INGREDIENTS: METHYL SALICYLATE; CYCLOMETHICONE; BIS-ETHOXYDIGLYCOL CYCLOHEXANE 1,4-DICARBOXYLATE; HARPAGOPHYTUM PROCUMBENS ROOT; ISOPROPYL PALMITATE; LEMON OIL; EAST INDIAN LEMONGRASS OIL; PEPPERMINT OIL; TEA TREE OIL; ARNICA MONTANA FLOWER; 1-(3-AMINO-4-HYDROXYPHENYL)-2-((2-(4-METHOXYPHENYL)-1-METHYLETHYL)AMINO)ETHANOL; PINUS RESINOSA WHOLE; EUCALYPTUS OIL; PROPYLENE GLYCOL 1-ALLYL ETHER

RelieveIt Footspray

Drug Facts

Active Ingredient

Menthol 8.0%

Purpose

External analgesic

Uses

For temporary relief of minor aches and pains of muscles, joints and feet.

Warnings

for external use only

When using this product: use only as directed• avoid contact with eyes or mucous membrane• do not apply to open wounds, damaged or very sensitive skin • Do not use if you are allergic to any of this product's Active or Inactive ingredients

PREGNANCY OR BREAST FEEDING

If pregnant or breast-feeding, ask a health professional before use.

Keep out of reach of children. If swallowed, get medical help or contact a Poison Control Center right away.

Directions

• Spray balls of feet. arches, heels, toes and legs on bare skin before starting your day or activity:

6 - 8 sprays each foot· Apply generously when wearing stockings; 8+ sprays each foot

• Let dry completely • Apply again as needed for extended relief

Children under 2: consult a doctor before use

Directions

• Spray balls of feet. arches, heels, toes and legs on bare skin before starting your day or activity:

6 - 8 sprays each foot· Apply generously when wearing stockings; 8+ sprays each foot

• Let dry completely • Apply again as needed for extended relief

Children under 2: consult a doctor before use

Inactive ingredients

Arnica Montona, Cyclomethicone, Ethyl Alcohol. Ethoxydiglycol. Eucalyptus Oil. Horpogophytum. lsopropyl Palmitate, Lemon Oil, Lemongrass Oil, Pinus Resin, Propylene Glycol, Peppermint Oil, Teo Tree Oil, Wintergreen Oil

Manufactured for: SprainGo, LLC

3802 Spectrum Blvd, Suite 112E

Tampa, FL 33612

Made in the USA

Other Information

• Do not use if the package seal is broken• Store at 68-77°F (20 -25°)

• Keep this package. It contains important information on directions for use